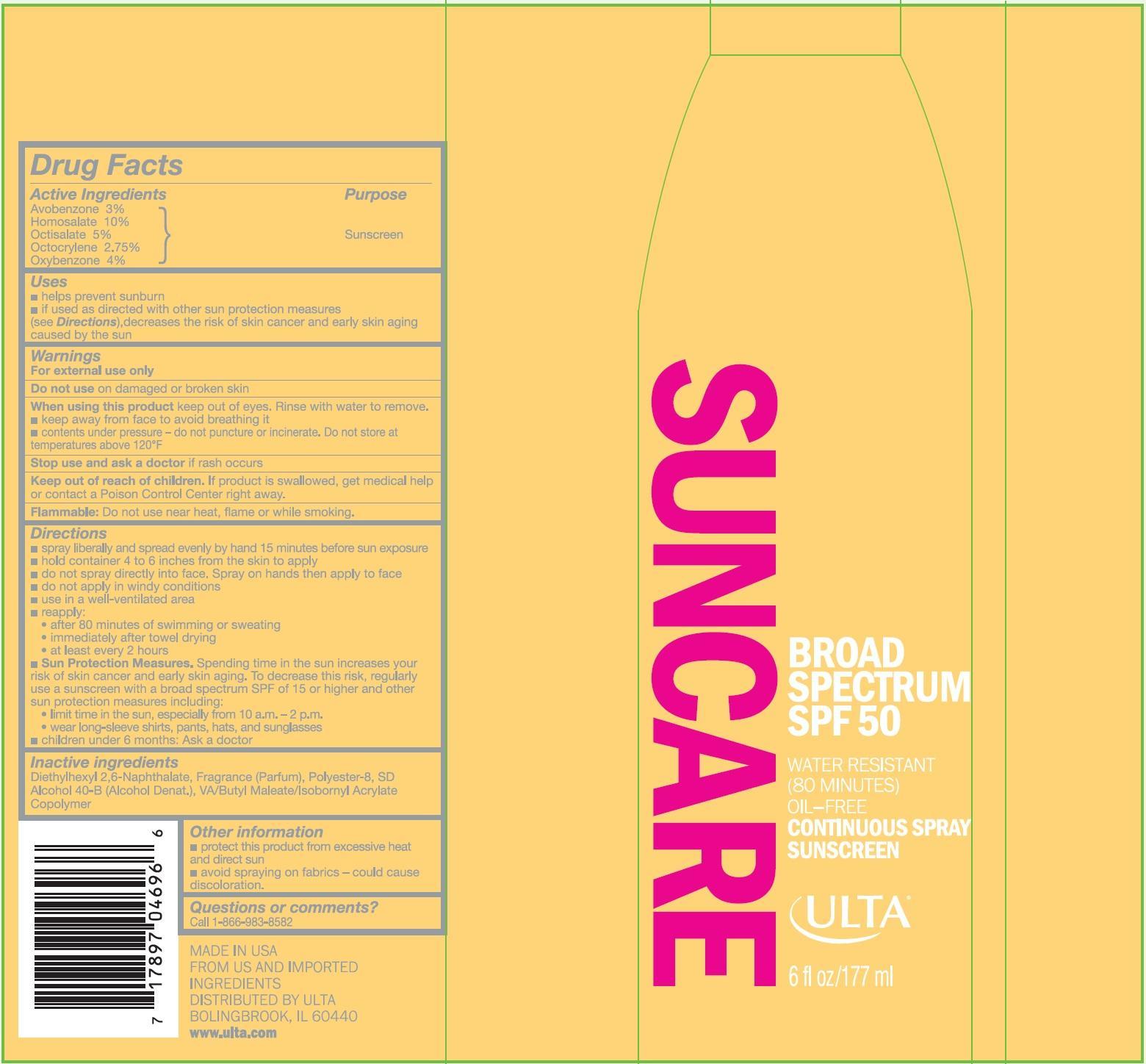 DRUG LABEL: Ulta
NDC: 13630-0070 | Form: SPRAY
Manufacturer: Prime Packaging, Inc.
Category: otc | Type: HUMAN OTC DRUG LABEL
Date: 20200117

ACTIVE INGREDIENTS: AVOBENZONE 25.4 mg/1 mL; HOMOSALATE 84.8 mg/1 mL; OCTISALATE 42.4 mg/1 mL; OCTOCRYLENE 23.3 mg/1 mL; OXYBENZONE 33.9 mg/1 mL
INACTIVE INGREDIENTS: DIETHYLHEXYL 2,6-NAPHTHALATE; POLYESTER-8 (1400 MW, CYANODIPHENYLPROPENOYL CAPPED); ALCOHOL; DIBUTYL MALEATE

Active ingredients

Avobenzone 3%, Homosalate 10 %, Octisalate 5 %, Octocrylene 2.75 %, and Oxybenzone 4 %

Purpose

Sunscreen

Uses

- helps prevent sunburn
- If used as directed with other sun protection measures (see Directions), decreases the risk of skin cancer and early skin aging caused by the sun

Warnings

OTHER SAFETY INFORMATION

For external use only

Do not use on broken or damaged skin

When using this product keep out of eyes. Rinse with water to remove.

- keep away from face to avoid breathing it.
- contents under pressure - do not puncture or incinirate. Do not store at temperatures above 120^0F

Stop use and ask a doctor if rash occurs.

Keep out of reach of children. If product is swallowed, get medical help or contact a Poison Control Center right away.

OTHER SAFETY INFORMATION

Flammable: Do not use near heat, flame or while smoking

Directions

- spray liberally and spread evenly by hand 15 minutes before sun exposure
- hold container 4 to 6 inches from the skin to apply
- do not spray directly on face. Spray on hands then apply to face
- do not apply in windy conditions
- use in well-ventilated areas
- reapply:
  - after 80 minutes of swimming or sweating
  - immediately after towel drying
  - at least every 2 hours
- Sun Protection Measures. Spending time in the sun increases your risk of skin cancer and early skin aging. To decrease this risk, regularly use a sunscreen with broad spectrum SPF of 15 or higher and other sun protection measures including:
  - limit time in the sun, especially from 10 a.m. – 2 p.m.
  - wear long-sleeve shirts, pants, hats, and sunglasses
- Children under 6 months: Ask a doctor

Inactive Ingredients

Diethylhexyl 2,6-Naphthalate, Fragrance (Parfum), Polyester-8, SD Alcohol 40-B, VA/Butyl Maleate/Isobornyl Acrylate Copolymer

Other information

- protect this product from excesive heat and direct sun
- avoid spraying on fabrics - could cause discoloration

Questions or Comments?

Call toll free 1-866-983-8582

PRINCIPAL DISPLAY PANEL - 177 mL Can Label

SUNCARE

BROAD SPECTRUM

SPF 50

WATER RESISTANT

(80 MINUTES)

OIL-FREE

CONTINUOUS SPRAY

SUNSCREEN

ULTA

6 fl oz./177 ml